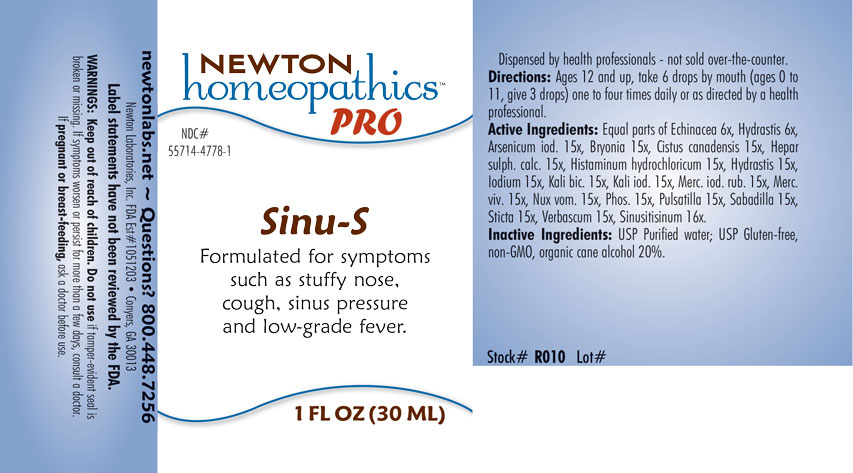 DRUG LABEL: Sinu-S
NDC: 55714-4778 | Form: LIQUID
Manufacturer: Newton Laboratories, Inc.
Category: homeopathic | Type: HUMAN OTC DRUG LABEL
Date: 20201207

ACTIVE INGREDIENTS: ECHINACEA, UNSPECIFIED 6 [hp_X]/1 mL; SCHOENOCAULON OFFICINALE SEED 15 [hp_X]/1 mL; ARSENIC TRIOXIDE 15 [hp_X]/1 mL; BRYONIA ALBA ROOT 15 [hp_X]/1 mL; HELIANTHEMUM CANADENSE 15 [hp_X]/1 mL; CALCIUM SULFIDE 15 [hp_X]/1 mL; HISTAMINE DIHYDROCHLORIDE 15 [hp_X]/1 mL; IODINE 15 [hp_X]/1 mL; POTASSIUM DICHROMATE 15 [hp_X]/1 mL; POTASSIUM IODIDE 15 [hp_X]/1 mL; MERCURIC IODIDE 15 [hp_X]/1 mL; MERCURY 15 [hp_X]/1 mL; STRYCHNOS NUX-VOMICA SEED 15 [hp_X]/1 mL; PHOSPHORUS 15 [hp_X]/1 mL; ANEMONE PULSATILLA 15 [hp_X]/1 mL; VERBASCUM THAPSUS 15 [hp_X]/1 mL; SINUSITISINUM 16 [hp_X]/1 mL; LOBARIA PULMONARIA 15 [hp_X]/1 mL; GOLDENSEAL 15 [hp_X]/1 mL
INACTIVE INGREDIENTS: WATER; ALCOHOL

Sinu-S 4778L

INDICATIONS & USAGE SECTION

Formulated for symptoms such as stuffy nose, cough, sinus pressure and low-grade fever.

DOSAGE & ADMINISTRATION SECTION

Directions: Ages 12 and up, take 6 drops by mouth (ages 0 to 11, give 3 drops) one to four times daily or as directed by a health professional.

OTC - ACTIVE INGREDIENT SECTION

Equal parts of Echinacea 6x, Hydrastis canadensis 6x, Arsenicum iodatum 15x, Bryonia 15x, Cistus canadensis 15x, Hepar sulphuris calcareum 15x, Histaminum hydrochloricum 15x, Hydrastis canadensis 15x, Iodium 15x, Kali bichromicum 15x, Kali iodatum 15x, Mercurius iodatus ruber 15x, Mercurius vivus 15x, Nux vomica 15x, Phosphorus 15x, Pulsatilla 15x, Sabadilla 15x, Sticta pulmonaria 15x, Verbascum thapsus 15x, Sinusitisinum 16x.

OTC - PURPOSE SECTION

Formulated for symptoms such as stuffy nose, cough, sinus pressure and low-grade fever.

INACTIVE INGREDIENT SECTION

I nactive Ingredients: USP Purified water; USP Gluten-free, non-GMO, organic cane alcohol 20%.

QUESTIONS SECTION

newtonlabs.net - Questions? 800.448.7256

Newton Laboratories, Inc. FDA Est # 1051203 Conyers, GA 30013

WARNINGS SECTION

WARNINGS: Keep out of reach of children. Do not use if tamper-evident seal is broken or missing. If symptoms worsen or persist for more than a few days, consult a doctor. If pregnant or breast-feeding, ask a doctor before use.

OTC - PREGNANCY OR BREAST FEEDING SECTION

If pregnant or breast-feeding, ask a doctor before use.

OTC - KEEP OUT OF REACH OF CHILDREN

Keep out of reach of children.